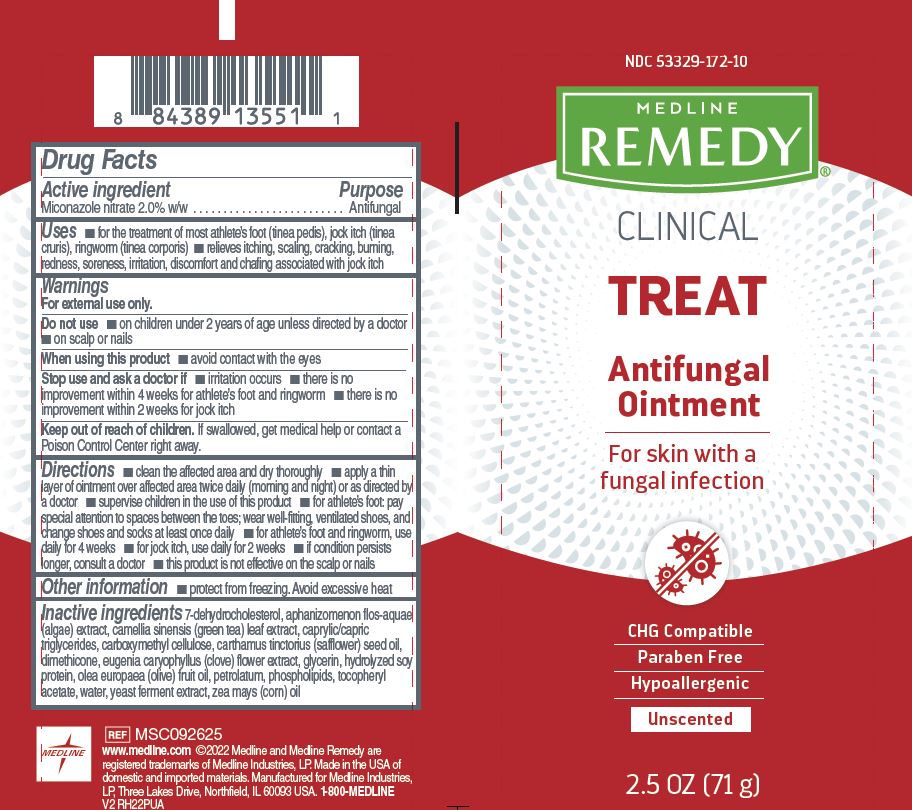 DRUG LABEL: Medline
NDC: 53329-172 | Form: OINTMENT
Manufacturer: Medline Industries, LP
Category: otc | Type: HUMAN OTC DRUG LABEL
Date: 20251103

ACTIVE INGREDIENTS: MICONAZOLE NITRATE 2 g/100 g
INACTIVE INGREDIENTS: GREEN TEA LEAF; CARBOXYMETHYLCELLULOSE; 7-DEHYDROCHOLESTEROL; MEDIUM-CHAIN TRIGLYCERIDES; DIMETHICONE; CLOVE; HYDROLYZED SOY PROTEIN (ENZYMATIC; 2000 MW); GLYCERIN; PETROLATUM; HYDROGENATED SOYBEAN LECITHIN; ALPHA-TOCOPHEROL ACETATE; YEAST, UNSPECIFIED; CORN OIL; APHANIZOMENON FLOSAQUAE; OLIVE OIL; WATER; SAFFLOWER SEED OIL POLYGLYCERYL-6 ESTERS

172 Remedy Clinical Antifungal Ointment

Active ingredient

Miconazole nitrate 2.0% w/w

Purpose

Antifungal

Uses

- for the treatment of most athlete's foot (tinea pedis), jock itch (tinea cruris), ringworm (tinea corporis)
- relieves itching, scaling, cracking, burning, redness, soreness, irritation, discomfort and chafing associated with jock itch

Warnings

For external use only.

Do not use

- on children under 2 years of age unless directed by a doctor
- on scalp or nails

When using this product

- avoid contact with eyes

Stop use and ask a doctor if

- irritation occurs
- there is no improvement within 4 weeks for athlete's foot and ringworm
- there is no improvement within 2 weeks for jock itch

Keep out of reach of children.

If swallowed, get medical help or contact a Poison Control Center right away.

Directions

- clean the affected area and dry thoroughly
- apply a thin layer of ointment over affected area twice daily (morning and night) or as directed by a doctor
- supervise children in the use of this product
- for athlete’s foot: pay special attention to spaces between the toes; wear well-fitting, ventilated shoes, and change shoes and socks at least once daily
- for athlete’s foot and ringworm, use daily for 4 weeks
- for jock itch, use daily for 2 weeks
- if condition persists longer, consult a doctor
- this product is not effective on the scalp or nails

Other information

- protect from freezing
- avoid excessive heat

Inactive ingredient

7-dehydrocholesterol, aphanizomenon flos-aquae (algae) extract, camellia sinensis (green tea) leaf extract, caprylic/capric triglycerides, carboxymethyl cellulose, carthamus tinctorius (safflower) seed oil, dimethicone, eugenia caryophyllus (clove) flower extract, glycerin, hydrolyzed soy protein, olea europaea (olive) fruit oil, petrolatum, phospholipids, tocopheryl acetate, water, yeast ferment extract, zea mays (corn) oil

Manufacturing Information

www.medline.com

©2022 Medline and Medline Remedy are

registered trademarks of Medline Industries, LP.

Made in the USA of domestic and imported materials

Manufactured for Medline Industries, LP

Three Lakes Drive, Northfield, IL 60093 USA

1-800-MEDLINE

REF: MSC092625